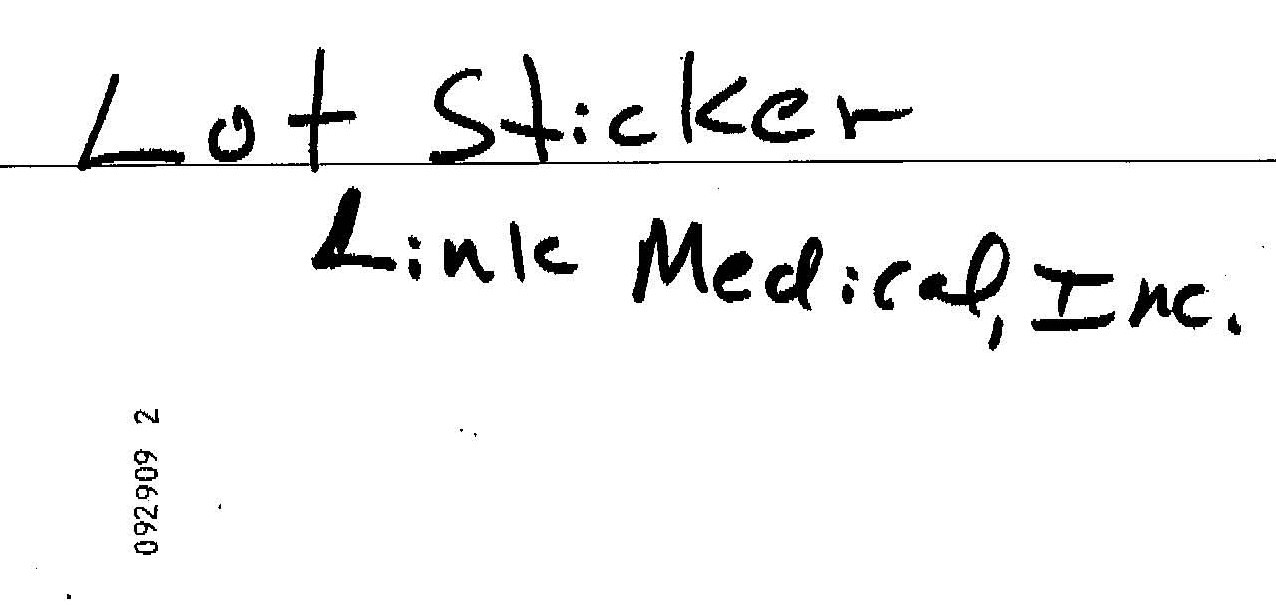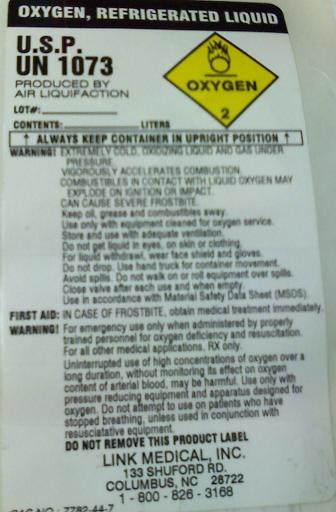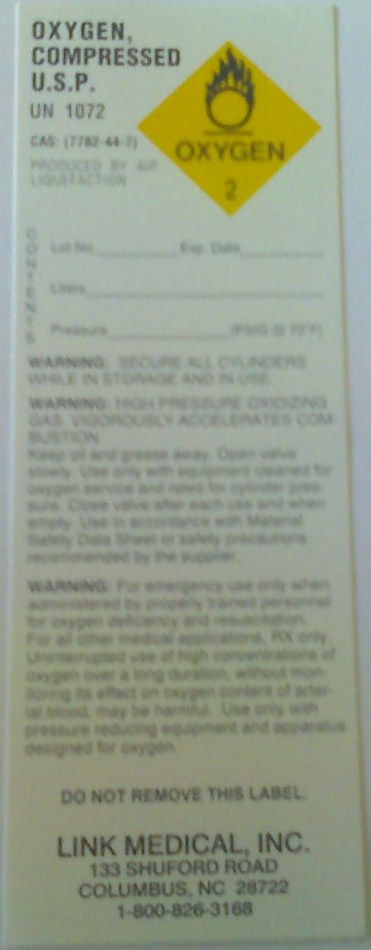 DRUG LABEL: Oxygen
NDC: 59877-0001 | Form: GAS
Manufacturer: Link Medical, Inc.
Category: prescription | Type: HUMAN PRESCRIPTION DRUG LABEL
Date: 20090930

ACTIVE INGREDIENTS: Oxygen 99 L/100 L

Oxygen